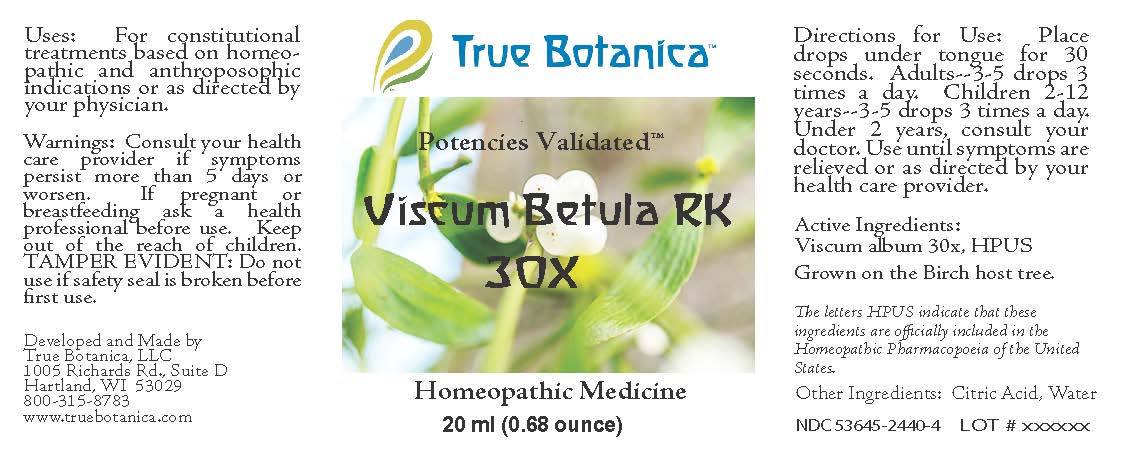 DRUG LABEL: Viscum Betula RK 30X
NDC: 53645-2440 | Form: LIQUID
Manufacturer: True Botanica, LLC
Category: homeopathic | Type: HUMAN OTC DRUG LABEL
Date: 20250710

ACTIVE INGREDIENTS: VISCUM ALBUM WHOLE 30 [hp_X]/20 mL
INACTIVE INGREDIENTS: CITRIC ACID MONOHYDRATE; WATER

Viscum Betula RK 30X

ACTIVE INGREDIENT

Viscum Album 30X, HPUS

The letters HPUS indicate that these ingredients are officially included in the Homeopathic Pharmacopoeia of the United States.

PURPOSE

For contitutional treatments based on homeopathic and anthroposophic indications or as directed by your physician.

Use:

For contitutional treatments based on homeopathic and anthroposophic indications or as directed by your physician.

Warnings:

Consult your health care provider if symptoms persist more than 5 days or worsen.

PREGNANCY OR BREAST FEEDING

If pregnant or breastfeeding ask a health professional before use.

Keep out of the reach of children.

DO NOT USE

TAMPER EVIDENT: Do not use if safety seal is broken before first use.

Directions for Use:

Place drops under tongue for 30 seconds. Adults 3-5 drops 3 times a day. Children 2-12 years--3-5 drops 3 times a day. Under 2 years, consult your doctor. Use until symptoms are relieved or as directed by your health care provider.

Other Ingredients:

Citric Acid, Water

QUESTIONS

Developed and Made by

True Botanica, LLC

1005 Richards Rd., Suite D

Hartland, WI 53029

800-315-8783

www.truebotanica.com